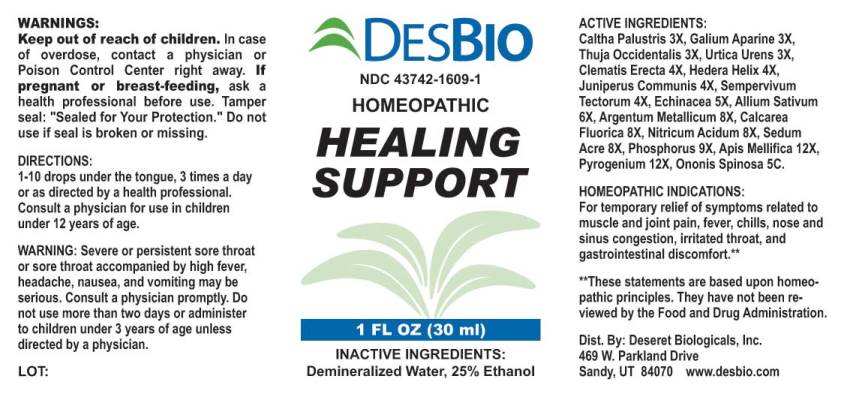 DRUG LABEL: Healing Support
NDC: 43742-1609 | Form: LIQUID
Manufacturer: Deseret Biologicals, Inc.
Category: homeopathic | Type: HUMAN OTC DRUG LABEL
Date: 20210628

ACTIVE INGREDIENTS: CALTHA PALUSTRIS 3 [hp_X]/1 mL; GALIUM APARINE 3 [hp_X]/1 mL; THUJA OCCIDENTALIS LEAFY TWIG 3 [hp_X]/1 mL; URTICA URENS 3 [hp_X]/1 mL; CLEMATIS RECTA FLOWERING TOP 4 [hp_X]/1 mL; HEDERA HELIX FLOWERING TWIG 4 [hp_X]/1 mL; JUNIPER BERRY 4 [hp_X]/1 mL; SEMPERVIVUM TECTORUM LEAF 4 [hp_X]/1 mL; ECHINACEA ANGUSTIFOLIA 5 [hp_X]/1 mL; GARLIC 6 [hp_X]/1 mL; SILVER 8 [hp_X]/1 mL; CALCIUM FLUORIDE 8 [hp_X]/1 mL; NITRIC ACID 8 [hp_X]/1 mL; SEDUM ACRE 8 [hp_X]/1 mL; PHOSPHORUS 9 [hp_X]/1 mL; APIS MELLIFERA 12 [hp_X]/1 mL; RANCID BEEF 12 [hp_X]/1 mL; ONONIS SPINOSA WHOLE 5 [hp_C]/1 mL
INACTIVE INGREDIENTS: WATER; ALCOHOL

Drug Facts:

ACTIVE INGREDIENTS:

Caltha Palustris 3X, Galium Aparine 3X, Thuja Occidentalis 3X, Urtica Urens 3X, Clematis Erecta 4X, Hedera Helix 4X, Juniperus Communis 4X, Sempervivum Tectorum 4X, Echinacea (Angustifolia) 5X, Allium Sativum 6X, Argentum Metallicum 8X, Calcarea Fluorica 8X, Nitricum Acidum 8X, Sedum Acre 8X, Phosphorus 9X, Apis Mellifica 12X, Pyrogenium 12X, Ononis Spinosa 5C.

HOMEOPATHIC INDICATIONS:

For temporary relief of symptoms related to muscle and joint pain, fever, chills, nose and sinus congestion, irritated throat, and gastrointestinal discomfort.**

**These statements are based upon homeopathic principles. They have not been reviewed by the Food and Drug Administration.

WARNINGS:

Keep out of reach of children. In case of overdose, contact a physician or Poison Control Center right away.

If pregnant or breast-feeding, ask a health professional before use.

Tamper seal: "Sealed for Your Protection." Do not use if seal is broken or missing.

Keep out of reach of children. In case of overdose, contact a physician or Poison Control Center right away.

DIRECTIONS:

1-10 drops under the tongue, 3 times a day or as directed by a health professional. Consult a physician for use in children under 12 years of age.

HOMEOPATHIC INDICATIONS:

For temporary relief of symptoms related to muscle and joint pain, fever, chills, nose and sinus congestion, irritated throat, and gastrointestinal discomfort.**

**These statements are based upon homeopathic principles. They have not been reviewed by the Food and Drug Administration.

INACTIVE INGREDIENTS:

Demineralized Water, 25% Ethanol

QUESTIONS:

Dist. By: Deseret Biologicals, Inc.

469 W. Parkland Drive

Sandy, UT 84070 www.desbio.com

PACKAGE LABEL DISPLAY:

DESBIO

NDC 43742-1609-1

HOMEOPATHIC

HEALING

SUPPORT

1 FL OZ (30 ml)